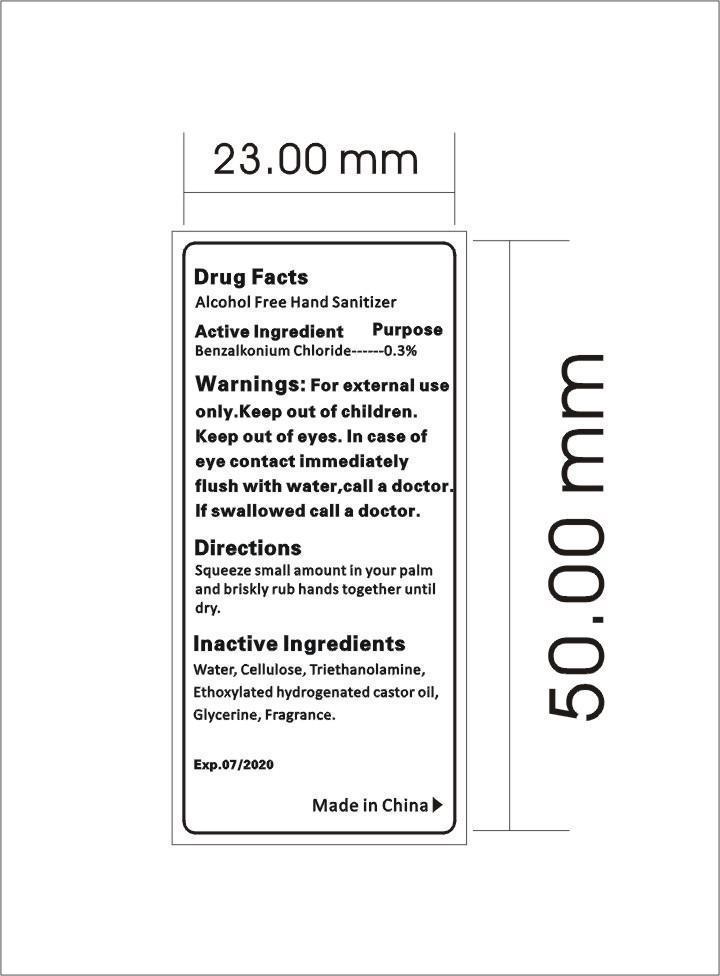 DRUG LABEL: Alcohol Free Hand Sanitizer
NDC: 47993-231 | Form: LIQUID
Manufacturer: NINGBO JIANGBEI OCEAN STAR TRADING CO.,LTD
Category: otc | Type: HUMAN OTC DRUG LABEL
Date: 20171206

ACTIVE INGREDIENTS: BENZALKONIUM CHLORIDE 0.3 g/100 g
INACTIVE INGREDIENTS: WATER 94.7 g/100 g; ALPHA CELLULOSE 1.4 g/100 g; TROLAMINE 1 g/100 g; HYDROGENATED CASTOR OIL 0.4 g/100 g; GLYCERIN 2 g/100 g; AROMADENDRIN 0.2 g/100 g

Active Ingredients

Active ingredients--------------purpose

Benzalkonium Chloride..........0.3%

Uses:
Keep skin Clean. Recommended for repeated use.

Warnings:

For external use only.Keep out of eyes.In case of eye contact immediately flush with water,call a doctor.If swallowed call a doctor.

Directions:

Squeeze small amount in your palm and briskly rub hands together until dry.

Other Information

Do not store above 110F(43C) May discolor certain fabric or surfaces. Harmful to wood finishes and plastics.

KEEP OUT OF REACH OF CHILDREN

Children under 6 years of age should be super vised when using this product.

Inactive Ingredients:

Water,Cellulose,Triethanolamine,Ethoxylated hydrogenated castor oil,Glycerine,Fragrance